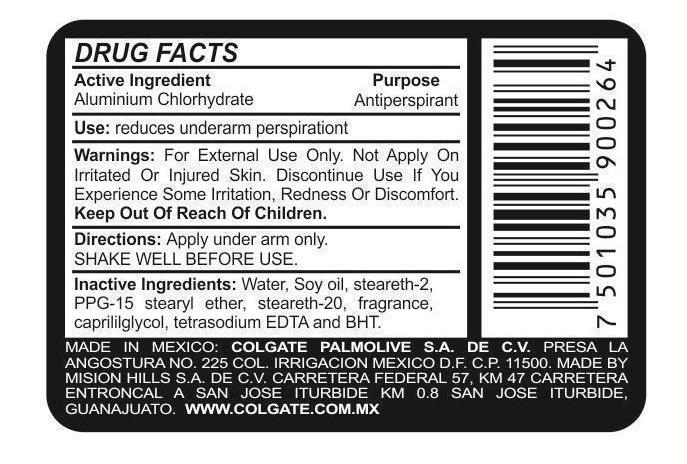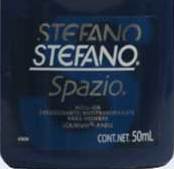 DRUG LABEL: Stefano Spazio
NDC: 69772-020 | Form: LIQUID
Manufacturer: Teresa Cecena DBA Genesis
Category: otc | Type: HUMAN OTC DRUG LABEL
Date: 20150602

ACTIVE INGREDIENTS: ALUMINUM CHLOROHYDRATE 25 g/100 mL
INACTIVE INGREDIENTS: WATER; STEARETH-2; PPG-15 STEARYL ETHER; CAPRYLYL GLYCOL; EDETATE SODIUM; BUTYLATED HYDROXYTOLUENE

ACTIVE INGREDIENT

Aluminum chlorohydrate

Purpose

Antiperspirant

Keep outt of the reach of children

USE

Reduces underarm persperation

WARNINGS AND PRECAUTIONS

FOR EXTERNAL USE ONLY DO NOT APPLY ON IRRITATED OR INJURED SKIN.

Discontinue use if you experience some irritation, redness or discomfort.

Directions

Apply under arm only.

Shake well before use.

INACTIVE INGREDIENT

Water, soyoil, stearth-2,PPG-15 stearyl ether, Steareth-20,fragance,caprylyl glycol, tetrasodium EDTA, and BHT

Use

Reduces underarm persperation